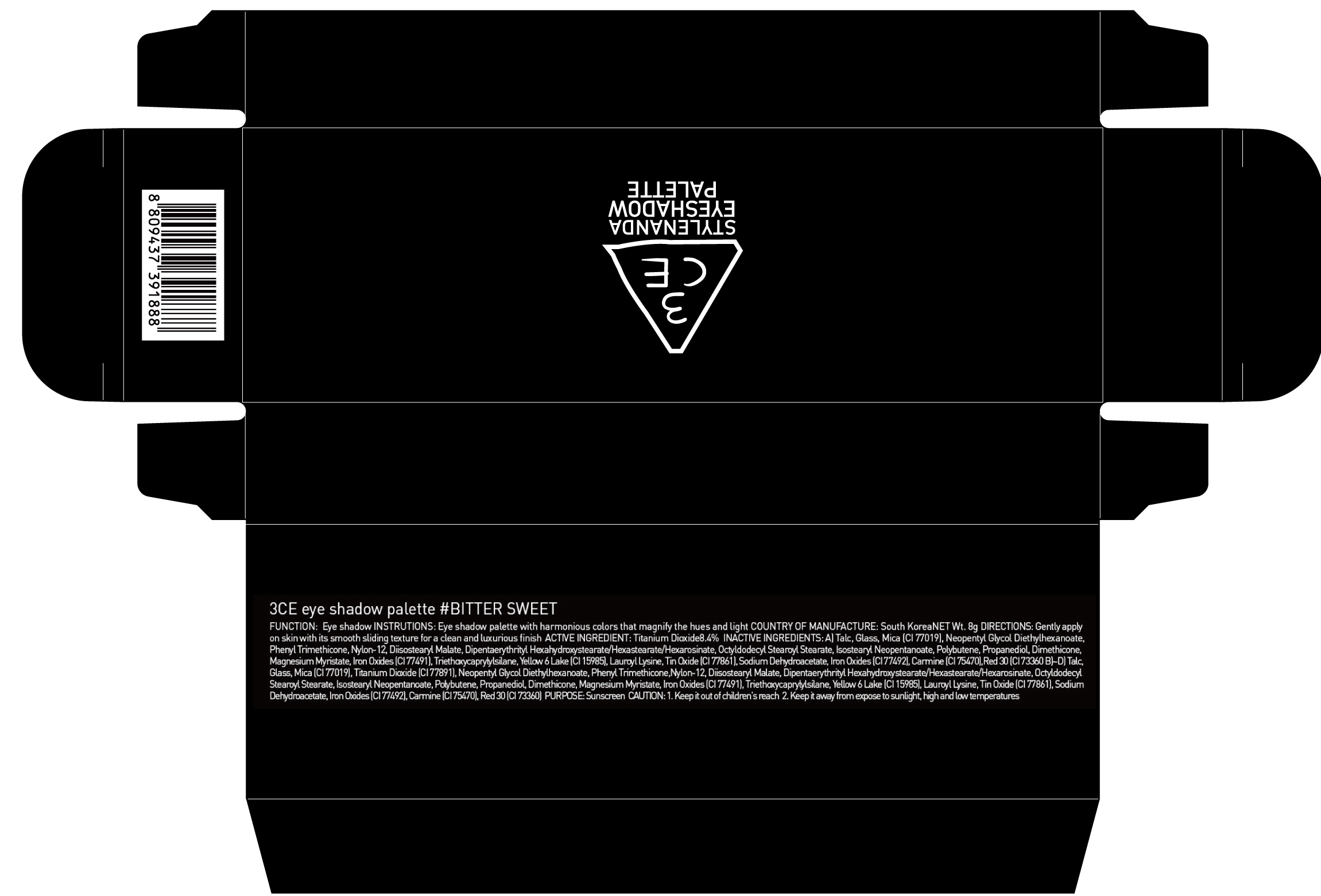 DRUG LABEL: 3CE EYE SHADOW PALETTE BITTER SWEET
NDC: 60764-064 | Form: POWDER
Manufacturer: Nanda Co., Ltd
Category: otc | Type: HUMAN OTC DRUG LABEL
Date: 20161004

ACTIVE INGREDIENTS: Titanium Dioxide 0.67 g/8 g
INACTIVE INGREDIENTS: Talc; Mica

ACTIVE INGREDIENT

Active Ingredient: Titanium Dioxide 8.4%

INACTIVE INGREDIENT

Inactive Ingredients:

A) Talc, Glass, Mica (CI 77019), Neopentyl Glycol Diethylhexanoate, Phenyl Trimethicone, Nylon-12, Diisostearyl Malate, Dipentaerythrityl Hexahydroxystearate/Hexastearate/Hexarosinate, Octyldodecyl Stearoyl Stearate, Isostearyl Neopentanoate, Polybutene, Propanediol, Dimethicone, Magnesium Myristate, Iron Oxides (CI 77491), Triethoxycaprylylsilane, Yellow 6 Lake (CI 15985), Lauroyl Lysine, Tin Oxide (CI 77861), Sodium Dehydroacetate, Iron Oxides (CI 77492), Carmine (CI 75470), Red 30 (CI 73360)

B)~D) Talc, Glass, Mica (CI 77019), Titanium Dioxide (CI 77891), Neopentyl Glycol Diethylhexanoate, Phenyl Trimethicone,Nylon-12, Diisostearyl Malate, Dipentaerythrityl Hexahydroxystearate/Hexastearate/Hexarosinate, Octyldodecyl Stearoyl Stearate, Isostearyl Neopentanoate, Polybutene, Propanediol, Dimethicone, Magnesium Myristate, Iron Oxides (CI 77491), Triethoxycaprylylsilane, Yellow 6 Lake (CI 15985), Lauroyl Lysine, Tin Oxide (CI 77861), Sodium Dehydroacetate, Iron Oxides (CI 77492), Carmine (CI 75470), Red 30 (CI 73360)

PURPOSE

Purpose: Sunscreen

CAUTION

CAUTION: 1. Keep it out of children's reach 2. Keep it away from expose to sunlight, high and low temperatures.

DESCRIPTION

INSTRUCTIONS: Eye shadow palette with harmonious colors that magnify the hues and light.

Directions: Gently apply on skin with its smooth sliding texture for a clean and luxurious finish